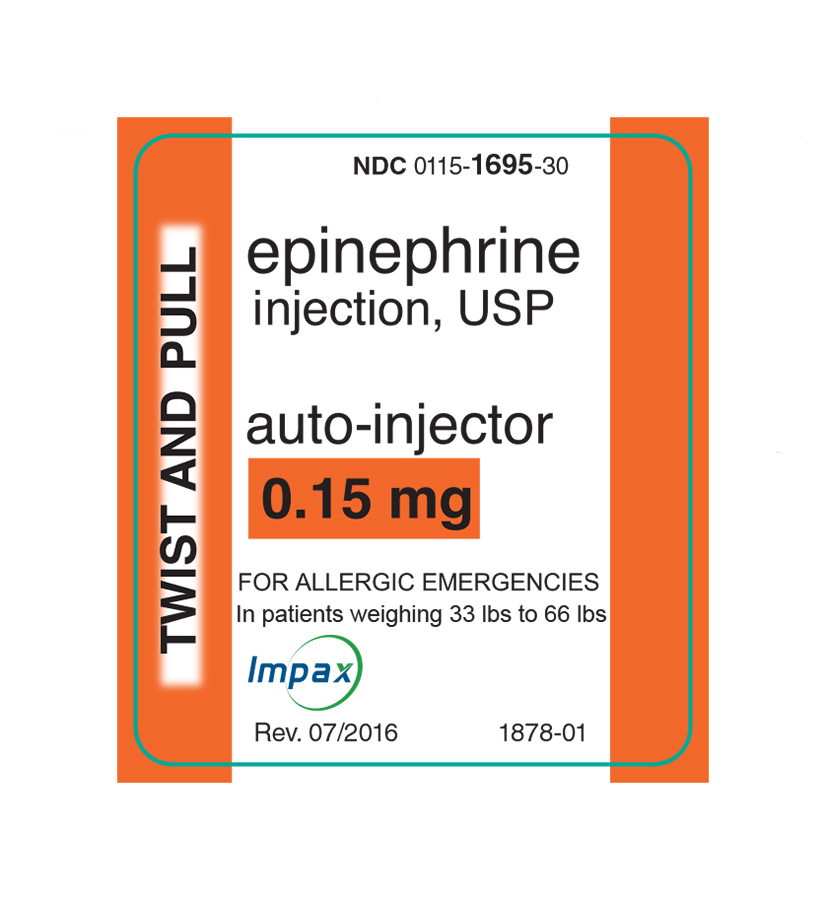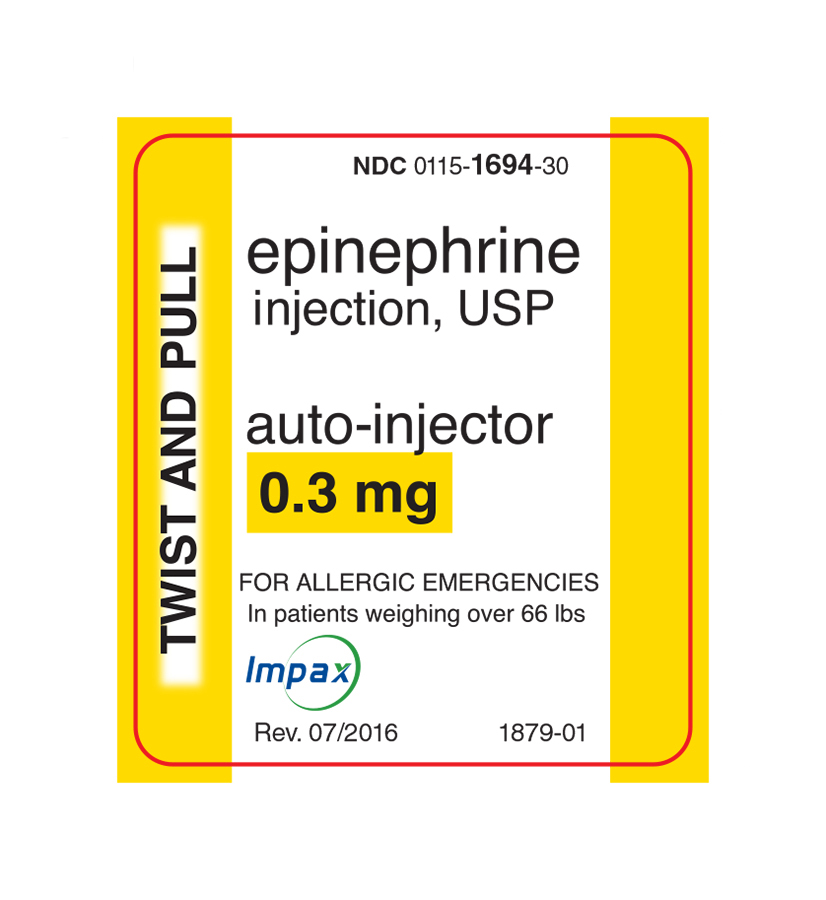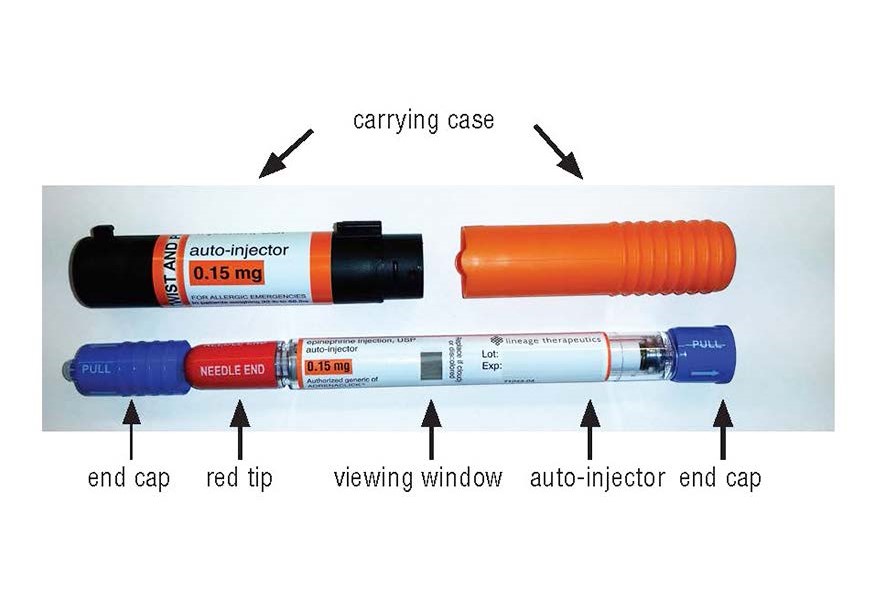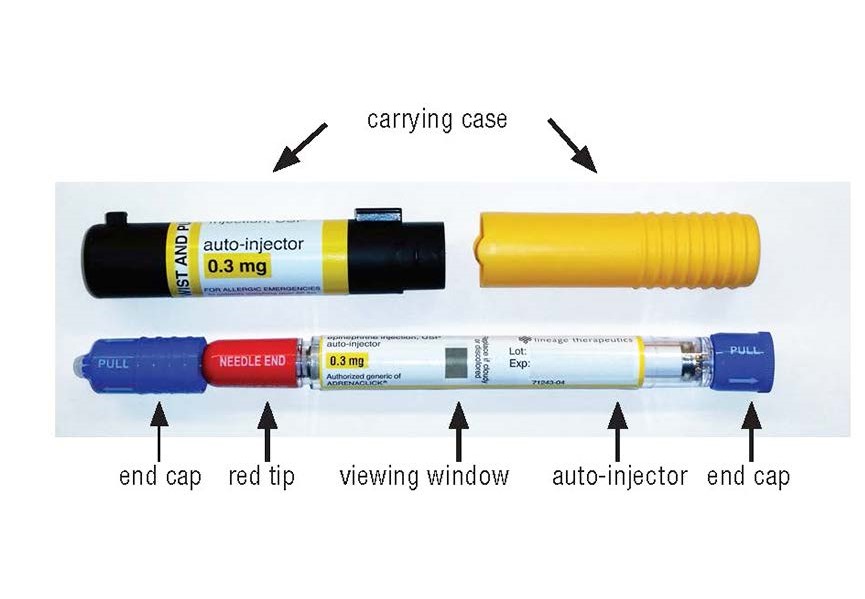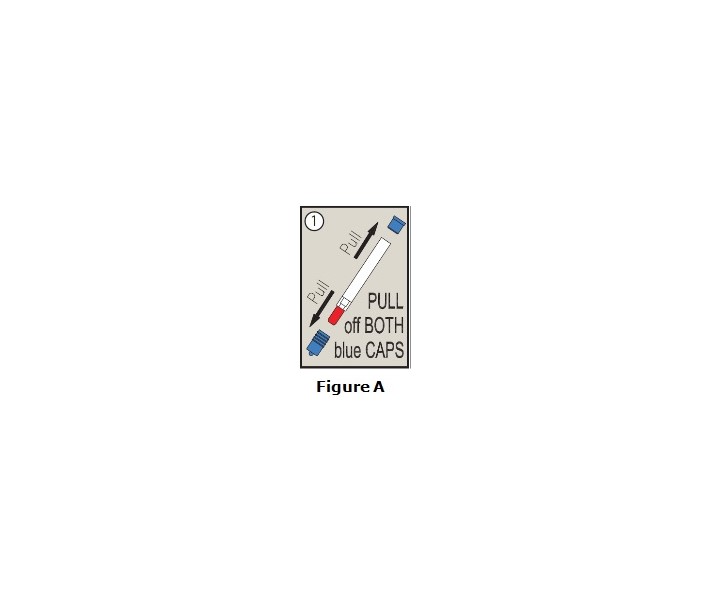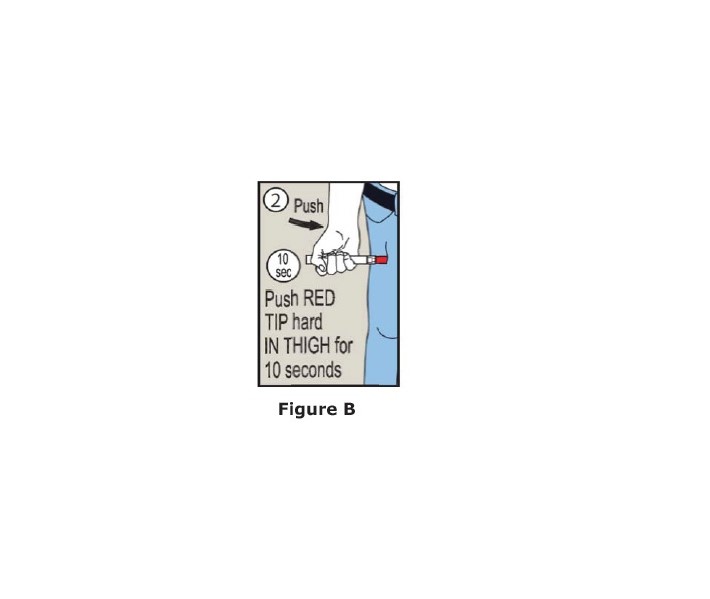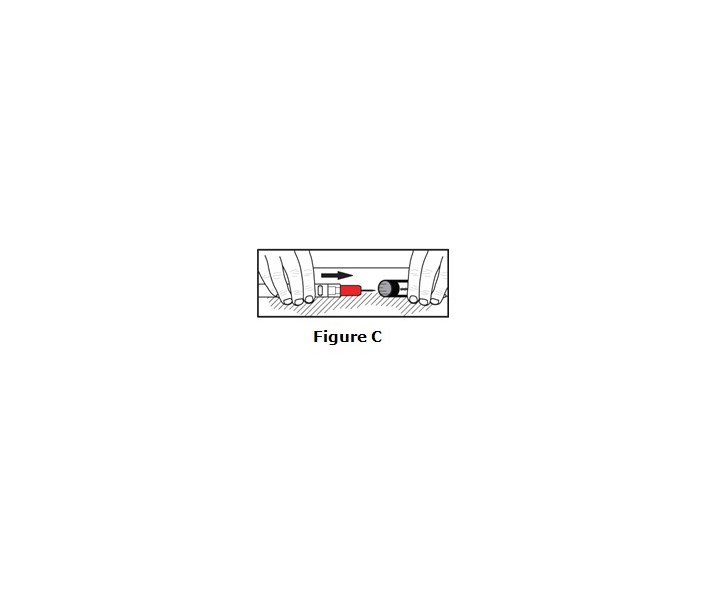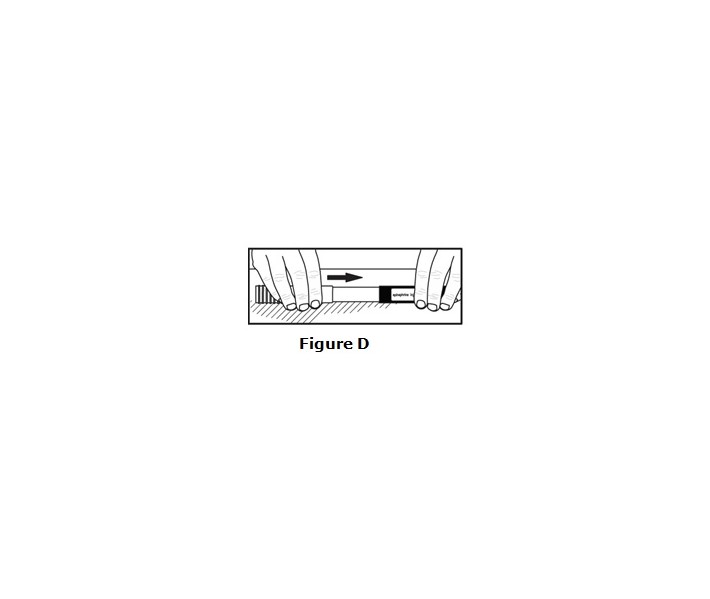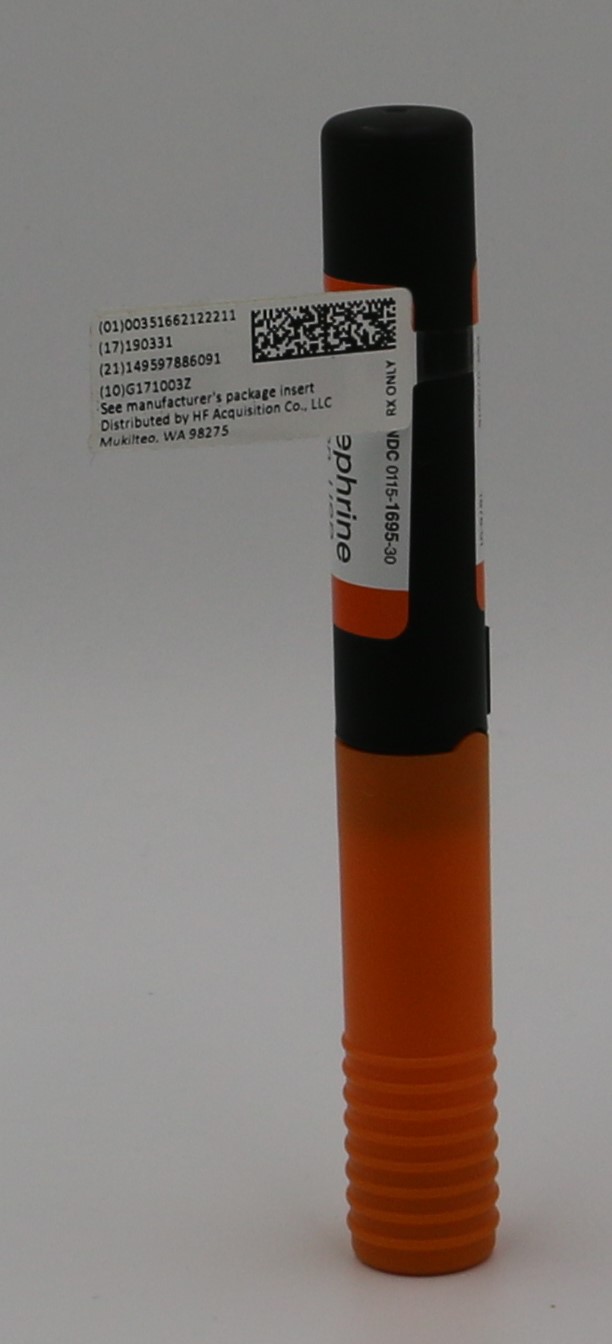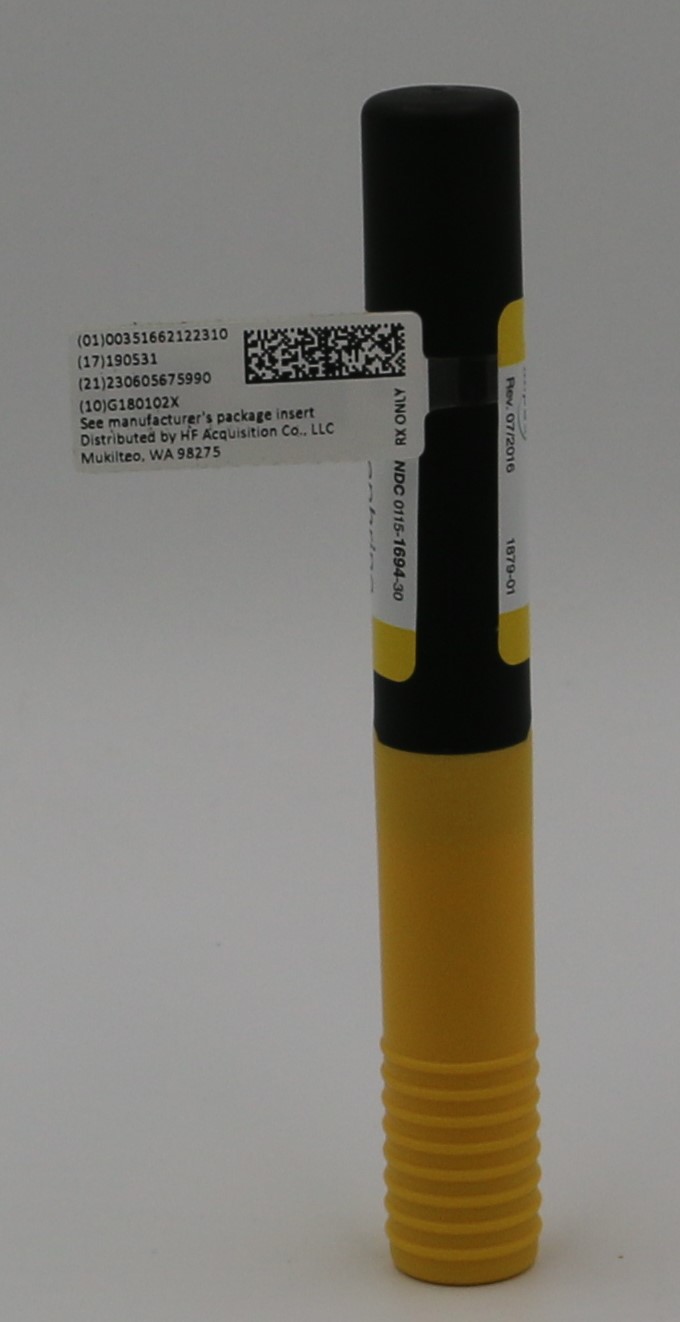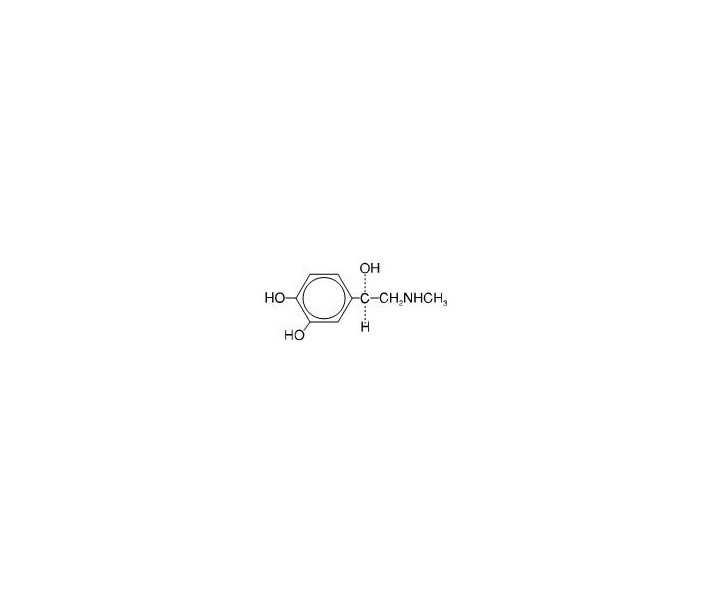 DRUG LABEL: EPINEPHRINE
NDC: 51662-1222 | Form: INJECTION
Manufacturer: HF Acquisition Co LLC, DBA HealthFirst
Category: prescription | Type: HUMAN PRESCRIPTION DRUG LABEL
Date: 20221209

ACTIVE INGREDIENTS: EPINEPHRINE 0.15 mg/0.15 mL
INACTIVE INGREDIENTS: HYDROCHLORIC ACID; SODIUM CHLORIDE; CHLOROBUTANOL; SODIUM BISULFITE; SODIUM HYDROXIDE

EPINEPHRINE INJECTION, USP AUTO INJECTOR

HIGHLIGHTS OF PRESCRIBING INFORMATION

These highlights do not include all the information needed to use EPINEPHRINE INJECTION, USP AUTO-INJECTOR safely and effectively. See full prescribing information for EPINEPHRINE INJECTION, USP AUTO-INJECTOR.
Epinephrine injection, USP auto-injector 0.3 mg, 0.15 mg, for intramuscular or subcutaneous use
Initial U.S. Approval: 1939

INDICATIONS AND USAGE

Epinephrine injection, USP auto-injector contains epinephrine, a non-selective alpha and beta-adrenergic receptor agonist, indicated in the emergency treatment of allergic reactions (Type I) including anaphylaxis. (1)

DOSAGE AND ADMINISTRATION

Patients greater than or equal to 30 kg (66 lbs): Epinephrine injection, USP auto-injector 0.3 mg (2)
Patients 15 to 30 kg (33 lbs-66 lbs): Epinephrine injection, USP auto-injector 0.15 mg (2)

Inject epinephrine injection, USP auto-injector intramuscularly or subcutaneously into the anterolateral aspect of the thigh, through clothing if necessary. Each device is a single-use injection. (2)

DOSAGE FORMS AND STRENGTHS

Injection, 0.3 mg: 0.3 mg/0.3 mL epinephrine injection, USP, pre-filled auto-injector (3)
Injection, 0.15 mg: 0.15 mg/0.15 mL epinephrine injection, USP, pre-filled auto-injector (3)

CONTRAINDICATIONS

None. (4)

WARNINGS AND PRECAUTIONS

In conjunction with use, seek immediate medical or hospital care. (5, 5.1)
Do not inject intravenously, into buttock, or into digits, hands, or feet. (5, 5.2)
To minimize the risk of injection related injury, instruct caregivers to hold the child’s leg firmly in place and limit movement prior to and during injection when administering to young children. (5, 5.2)
Rare cases of serious skin and soft tissue infections have been reported following epinephrine injection. Advise patients to seek medical care if they develop signs or symptoms of infection. (5, 5.3)
The presence of a sulfite in this product should not deter use. (5, 5.4)
Administer with caution in patients with heart disease; may aggravate angina pectoris or produce ventricular arrhythmias. (5, 5.5)

ADVERSE REACTIONS

Adverse reactions to epinephrine include anxiety, apprehensiveness, restlessness, tremor, weakness, dizziness, sweating, palpitations, pallor, nausea and vomiting, headache, and/or respiratory difficulties. (6)

To report SUSPECTED ADVERSE REACTIONS, contact Impax Laboratories, Inc. at 1-800-934-6729 or FDA at 1-800-FDA-1088 or www.fda.gov/medwatch.

DRUG INTERACTIONS

Cardiac glycosides or diuretics: observe for development of cardiac arrhythmias. (7)
Tricyclic antidepressants, monoamine oxidase inhibitors, levothyroxine sodium, and certain antihistamines: potentiate effects of epinephrine. (7)
Beta-adrenergic blocking drugs: antagonize cardiostimulating and bronchodilating effects of epinephrine. (7)
Alpha-adrenergic blocking drugs: antagonize vasoconstricting and hypertensive effects of epinephrine. (7)
Ergot alkaloids: may reverse the pressor effects of epinephrine. (7)

USE IN SPECIFIC POPULATIONS

Elderly patients may be at greater risk of developing adverse reactions. (5-5.5, 8-8.5)

See 17 for PATIENT COUNSELING INFORMATION and FDA-approved patient labeling.

Revised: 8/2018

FULL PRESCRIBING INFORMATION: CONTENTS*

1 INDICATIONS & USAGE
2 DOSAGE & ADMINISTRATION
3 DOSAGE FORMS & STRENGTHS
4 CONTRAINDICATIONS
5 WARNINGS & PRECAUTIONS
5.1 Emergency Treatment
5.2 Injection-Related Complications
5.3 Serious Infections at the Injection Site
5.4 Allergic Reactions Associated with Sulfite
5.5 Disease Interactions
6 ADVERSE REACTIONS
7 DRUG INTERACTIONS
8 USE IN SPECIFIC POPULATIONS
8.1 Pregnancy
8.3 Nursing Mothers
8.4 Pediatric Use
8.5 Geriatric Use
10 OVERDOSAGE
11 DESCRIPTION
12 CLINICAL PHARMACOLOGY
12.1 Mechanism of Action
12.2 Pharmacodynamics
13 NONCLINICAL TOXICOLOGY
13.1 Carcinogenesis, Mutagenesis, Impairment of Fertility
16 HOW SUPPLIED/STORAGE & HANDLINGHOW SUPPLIED/STORAGE AND HANDLING
16.1 How Supplied
16.2 Storage and Handling
17 PATIENT COUNSELING INFORMATION

INSTRUCTIONS FOR USE

*
Sections or subsections omitted from the full prescribing information are not listed.

1 INDICATIONS & USAGE

Epinephrine injection, USP auto-injector is indicated in the emergency treatment of allergic reactions (Type I) including anaphylaxis to stinging insects (e.g., order Hymenoptera, which includes bees, wasps, hornets, yellow jackets and fire ants), and biting insects (e.g., triatoma, mosquitoes), allergen immunotherapy, foods, drugs, diagnostic testing substances (e.g., radiocontrast media), and other allergens, as well as idiopathic anaphylaxis or exercise-induced anaphylaxis.

Epinephrine injection, USP auto-injector is intended for immediate administration in patients who are determined to be at increased risk for anaphylaxis, including individuals with a history of anaphylactic reactions.

Anaphylactic reactions may occur within minutes after exposure and consist of flushing, apprehension, syncope, tachycardia, thready or unobtainable pulse associated with a fall in blood pressure, convulsions, vomiting, diarrhea and abdominal cramps, involuntary voiding, wheezing, dyspnea due to laryngeal spasm, pruritus, rashes, urticaria, or angioedema.

Epinephrine injection, USP auto-injector is intended for immediate administration as emergency supportive therapy only and is not a replacement or substitute for immediate medical care.

2 DOSAGE & ADMINISTRATION

Selection of the appropriate epinephrine injection, USP auto-injector dosage strength is determined according to patient body weight.

Patients greater than or equal to 30 kg (approximately 66 pounds or more): epinephrine injection, USP auto-injector 0.3 mg
Patients 15 to 30 kg (33 pounds to 66 pounds): epinephrine injection, USP auto-injector 0.15 mg

Inject epinephrine injection, USP auto-injector intramuscularly or subcutaneously into the anterolateral aspect of the thigh, through clothing if necessary. Instruct caregivers of young children who are prescribed an epinephrine injection, USP auto-injector and who may be uncooperative and kick or move during an injection to hold the leg firmly in place and limit movement prior to and during an injection [see WARNINGS & PRECAUTIONS (5.2)].

Each epinephrine injection, USP auto-injector contains a single dose of epinephrine for single use injection. Since the doses of epinephrine delivered from epinephrine injection, USP auto-injector are fixed, consider using other forms of injectable epinephrine if doses lower than 0.15 mg are deemed necessary.

The prescriber should carefully assess each patient to determine the most appropriate dose of epinephrine, recognizing the life-threatening nature of the reactions for which this drug is indicated.

With severe persistent anaphylaxis, repeat injections with an additional epinephrine injection, USP auto-injector may be necessary. More than two sequential doses of epinephrine should only be administered under direct medical supervision [see WARNINGS & PRECAUTIONS (5.1)].

The epinephrine solution in the viewing window of epinephrine injection, USP auto-injector should be inspected visually for particulate matter and discoloration. Epinephrine is light sensitive and should be stored in the outer case provided to protect it from light [see HOW SUPPLIED/STORAGE & HANDLING (16.2)].

3 DOSAGE FORMS & STRENGTHS

Injection, 0.3 mg/0.3 mL epinephrine injection, USP, pre-filled auto-injector
Injection, 0.15 mg/0.15 mL epinephrine injection, USP, pre-filled auto-injector

4 CONTRAINDICATIONS

None.

5 WARNINGS & PRECAUTIONS

5.1 Emergency Treatment

Epinephrine injection, USP auto-injector is intended for immediate administration as emergency supportive therapy and is not intended as a substitute for immediate medical care. In conjunction with the administration of epinephrine, the patient should seek immediate medical or hospital care. More than two sequential doses of epinephrine should only be administered under direct medical supervision [see INDICATIONS & USAGE (1), DOSAGE & ADMINISTRATION (2) and PATIENT COUNSELING INFORMATION (17)].

5.2 Injection-Related Complications

Epinephrine injection, USP auto-injector should only be injected into the anterolateral aspect of the thigh [see DOSAGE & ADMINISTRATION (2) and PATIENT COUNSELING INFORMATION (17)].

Do not inject intravenously.

Large doses or accidental intravenous injection of epinephrine may result in cerebral hemorrhage due to a sharp rise in blood pressure. Rapidly acting vasodilators can counteract the marked pressor effects of epinephrine if there is such inadvertent administration.

Do not inject into buttock.

Injection into the buttock may not provide effective treatment of anaphylaxis. Advise the patient to go immediately to the nearest emergency room for further treatment of anaphylaxis. Additionally, injection into the buttock has been associated with the development of Clostridial infections (gas gangrene). Cleansing with alcohol does not kill bacterial spores, and therefore, does not lower the risk.

Do not inject into digits, hands or feet.

Since epinephrine is a strong vasoconstrictor, accidental injection into the digits, hands or feet may result in loss of blood flow to the affected area. Advise the patient to go immediately to the nearest emergency room and to inform the healthcare provider in the emergency room of the location of the accidental injection. Treatment of such inadvertent administration should consist of vasodilation, in addition to further appropriate treatment of anaphylaxis [see ADVERSE REACTIONS (6)].

Hold leg firmly during injection.

Lacerations, bent needles, and embedded needles have been reported when epinephrine has been injected into the thigh of young children who are uncooperative and kick or move during an injection. To minimize the risk of injection related injury when administering epinephrine injection, USP auto-injector to young children, instruct caregivers to hold the child’s leg firmly in place and limit movement prior to and during injection.

5.3 Serious Infections at the Injection Site

Rare cases of serious skin and soft tissue infections, including necrotizing fasciitis and myonecrosis caused by Clostridia (gas gangrene), have been reported at the injection site following epinephrine injection for anaphylaxis. Clostridium spores can be present on the skin and introduced into the deep tissue with subcutaneous or intramuscular injection. While cleansing with alcohol may reduce presence of bacteria on the skin, alcohol cleansing does not kill Clostridium spores. To decrease the risk of Clostridium infection, do not inject epinephrine injection, USP auto-injector into the buttock [see Warnings and Precautions (5.2)]. Advise patients to seek medical care if they develop signs or symptoms of infection, such as persistent redness, warmth, swelling, or tenderness, at the epinephrine injection site.

5.4 Allergic Reactions Associated with Sulfite

The presence of a sulfite in this product should not deter administration of the drug for treatment of serious allergic or other emergency situations even if the patient is sulfite-sensitive.

Epinephrine is the preferred treatment for serious allergic reactions or other emergency situations even though this product contains sodium bisulfite, a sulfite that may, in other products, cause allergic-type reactions including anaphylactic symptoms or life-threatening or less severe asthmatic episodes in certain susceptible persons.

The alternatives to using epinephrine in a life-threatening situation may not be satisfactory.

5.5 Disease Interactions

Some patients may be at greater risk for developing adverse reactions after epinephrine administration. Despite these concerns, it should be recognized that the presence of these conditions is not a contraindication to epinephrine administration in an acute, life-threatening situation. Therefore, patients with these conditions, and/or any other person who might be in a position to administer epinephrine injection, USP auto-injector to a patient experiencing anaphylaxis should be carefully instructed in regard to the circumstances under which epinephrine should be used.

Patients with Heart Disease
Epinephrine should be administered with caution to patients who have heart disease, including patients with cardiac arrhythmias, coronary artery or organic heart disease, or hypertension. In such patients, or in patients who are on drugs that may sensitize the heart to arrhythmias, epinephrine may precipitate or aggravate angina pectoris as well as produce ventricular arrhythmias [see DRUG INTERACTIONS (7) and ADVERSE REACTIONS (6)].

Other Patients and Diseases
Epinephrine should be administered with caution to patients with hyperthyroidism, diabetes, elderly individuals, and pregnant women. Patients with Parkinson's disease may notice a temporary worsening of symptoms.

6 ADVERSE REACTIONS

Due to the lack of randomized, controlled clinical trials of epinephrine for the treatment of anaphylaxis, the true incidence of adverse reactions associated with the systemic use of epinephrine is difficult to determine. Adverse reactions reported in observational trials, case reports, and studies are listed below.

Common adverse reactions to systemically administered epinephrine include anxiety; apprehensiveness; restlessness; tremor; weakness; dizziness; sweating; palpitations; pallor; nausea and vomiting; headache, and/or respiratory difficulties. These symptoms occur in some persons receiving therapeutic doses of epinephrine, but are more likely to occur in patients with hypertension or hyperthyroidism [see WARNINGS & PRECAUTIONS (5.5)].

Arrhythmias, including fatal ventricular fibrillation, have been reported, particularly in patients with underlying cardiac disease or those receiving certain drugs [see WARNINGS & PRECAUTIONS (5.5) and DRUG INTERACTIONS (7)].

Rapid rises in blood pressure have produced cerebral hemorrhage, particularly in elderly patients with cardiovascular disease [see WARNINGS & PRECAUTIONS (5.5)].

Angina may occur in patients with coronary artery disease [see WARNINGS & PRECAUTIONS (5.5)].

Accidental injection into the digits, hands or feet may result in loss of blood flow to the affected area [see WARNINGS & PRECAUTIONS (5.2)].

Adverse events experienced as a result of accidental injections may include increased heart rate, local reactions including injection site pallor, coldness and hypoesthesia or injury at the injection site resulting in bruising, bleeding, discoloration, erythema or skeletal injury.

Lacerations, bent needles, and embedded needles have been reported when epinephrine injection, USP auto-injector has been injected into the thigh of young children who are uncooperative and kick or move during an injection [see WARNINGS & PRECAUTIONS (5.2)].

Injection into the buttock has resulted in cases of gas gangrene [see WARNINGS & PRECAUTIONS (5.2)].

Rare cases of serious skin and soft tissue infections, including necrotizing fasciitis and myonecrosis caused by Clostridia (gas gangrene), have been reported following epinephrine injection in the thigh [see WARNINGS & PRECAUTIONS (5.3)].

Rare cases of stress cardiomyopathy have been reported in patients treated with epinephrine.

7 DRUG INTERACTIONS

Patients who receive epinephrine while concomitantly taking cardiac glycosides, diuretics, or anti-arrhythmics should be observed carefully for the development of cardiac arrhythmias [see WARNINGS & PRECAUTIONS (5.5)].

The effects of epinephrine may be potentiated by tricyclic antidepressants, monoamine oxidase inhibitors, levothyroxine sodium, and certain antihistamines, notably chlorpheniramine, tripelennamine, and diphenhydramine.

The cardiostimulating and bronchodilating effects of epinephrine are antagonized by beta-adrenergic blocking drugs, such as propranolol.

The vasoconstricting and hypertensive effects of epinephrine are antagonized by alpha-adrenergic blocking drugs, such as phentolamine.

Ergot alkaloids may also reverse the pressor effects of epinephrine.

8 USE IN SPECIFIC POPULATIONS

8.1 Pregnancy

Teratogenic Effects: Pregnancy Category C.

There are no adequate and well controlled studies of the acute effect of epinephrine in pregnant women.

Epinephrine was teratogenic in rabbits, mice and hamsters. Epinephrine should be used during pregnancy only if the potential benefit justifies the potential risk to the fetus (fetal anoxia, spontaneous abortion, or both).

Epinephrine has been shown to have teratogenic effects when administered subcutaneously in rabbits at approximately 30 times the maximum recommended daily subcutaneous or intramuscular dose (on a mg/m2 basis at a maternal dose of 1.2 mg/kg/day for two to three days), in mice at approximately 7 times the maximum daily subcutaneous or intramuscular dose (on a mg/m2 basis at a maternal subcutaneous dose of 1 mg/kg/day for 10 days), and in hamsters at approximately 5 times the maximum recommended daily subcutaneous or intramuscular dose (on a mg/m2 basis at a maternal subcutaneous dose of 0.5 mg/kg/day for 4 days).

These effects were not seen in mice at approximately 3 times the maximum recommended daily subcutaneous or intramuscular dose (on a mg/m2 basis at a subcutaneous maternal dose of 0.5 mg/kg/day for 10 days).

8.3 Nursing Mothers

It is not known whether epinephrine is excreted in human milk. Because many drugs are excreted in human milk, caution should be exercised when epinephrine injection, USP auto-injector is administered to a nursing woman.

8.4 Pediatric Use

Epinephrine injection, USP auto-injector may be administered to pediatric patients at a dosage appropriate to body weight [see Dosage and Administration (2)]. Clinical experience with the use of epinephrine suggests that the adverse reactions seen in children are similar in nature and extent to those both expected and reported in adults. Since the dose of epinephrine delivered from epinephrine injection, USP auto-injector is fixed, consider using other forms of injectable epinephrine if doses lower than 0.15 mg are deemed necessary.

8.5 Geriatric Use

Clinical studies for the treatment of anaphylaxis have not been performed in subjects aged 65 and over to determine whether they respond differently from younger subjects. However, other reported clinical experience with use of epinephrine for the treatment of anaphylaxis has identified that geriatric patients may be particularly sensitive to the effects of epinephrine. Therefore, epinephrine injection, USP auto-injector should be administered with caution in elderly individuals, who may be at greater risk for developing adverse reactions after epinephrine administration [see WARNINGS & PRECAUTIONS (5.5) and OVERDOSAGE (10)].

10 OVERDOSAGE

Overdosage of epinephrine may produce extremely elevated arterial pressure, which may result in cerebrovascular hemorrhage, particularly in elderly patients. Overdosage may also result in pulmonary edema because of peripheral vascular constriction together with cardiac stimulation. Treatment consists of a rapidly acting vasodilators or alpha-adrenergic blocking drugs and/or respiratory support.

Epinephrine overdosage can also cause transient bradycardia followed by tachycardia, and these may be accompanied by potentially fatal cardiac arrhythmias. Premature ventricular contractions may appear within one minute after injection and may be followed by multifocal ventricular tachycardia (prefibrillation rhythm). Subsidence of the ventricular effects may be followed by atrial tachycardia and occasionally by atrioventricular block. Treatment of arrhythmias consists of administration of a beta-adrenergic blocking drug such as propranolol.

Overdosage sometimes results in extreme pallor and coldness of the skin, metabolic acidosis, and kidney failure. Suitable corrective measures must be taken in such situations.

11 DESCRIPTION

Epinephrine injection, USP auto-injector 0.3 mg and 0.15 mg is an auto-injector and a combination product containing drug and device components.

Each epinephrine injection, USP auto-injector 0.3 mg delivers a single dose of 0.3 mg epinephrine from epinephrine injection, USP (0.3 mL) in a sterile solution.

Each epinephrine injection, USP auto-injector 0.15 mg delivers a single dose of 0.15 mg epinephrine from epinephrine injection, USP (0.15 mL) in a sterile solution.

Epinephrine injection, USP auto-injector 0.3 mg and epinephrine injection, USP auto-injector 0.15 mg each contain 1.1 mL of epinephrine solution. 0.3 mL and 0.15 mL epinephrine solution are dispensed for epinephrine injection, USP auto-injector 0.3 mg and epinephrine injection, USP auto-injector 0.15 mg, respectively, when activated. The solution remaining after activation is not available for future use and should be discarded.

Each 0.3 mL in epinephrine injection, USP auto-injector 0.3 mg contains 0.3 mg epinephrine, 2.6 mg sodium chloride, not more than 1.5 mg chlorobutanol, 0.45 mg sodium bisulfite, hydrochloric acid and sodium hydroxide to adjust pH, and water for injection. The pH range is 2.2-5.0.

Each 0.15 mL in epinephrine injection, USP auto-injector 0.15 mg contains 0.15 mg epinephrine, 1.3 mg sodium chloride, not more than 0.75 mg chlorobutanol, 0.225 sodium bisulfite, hydrochloric acid and sodium hydroxide to adjust pH, and water for injection. The pH range is 2.2-5.0.

Epinephrine is a sympathomimetic catecholamine. Chemically, epinephrine is (-)-3,4-Dihydroxy-α-[(methylamino)methyl]benzyl alcohol with the following structure:

Epinephrine solution deteriorates rapidly on exposure to air or light, turning pink from oxidation to adrenochrome and brown from the formation of melanin. Replace epinephrine injection, USP auto-injector if the epinephrine solution appears discolored (pinkish or brown color), cloudy, or contains particles.

Thoroughly review the patient instructions and operation of epinephrine injection, USP auto-injector with patients and caregivers prior to use [see PATIENT COUNSELING INFORMATION (17)].

12 CLINICALPHARMACOLOGY

12.1 Mechanism of Action

Epinephrine acts on both alpha- and beta-adrenergic receptors.

12.2 Pharmacodynamics

Through its action on alpha-adrenergic receptors, epinephrine lessens the vasodilation and increased vascular permeability that occurs during anaphylaxis, which can lead to loss of intravascular fluid volume and hypotension.

Through its action on beta-adrenergic receptors, epinephrine causes bronchial smooth muscle relaxation and helps alleviate bronchospasm, wheezing, and dyspnea that may occur during anaphylaxis.

Epinephrine also alleviates pruritus, urticaria, and angioedema, and may relieve gastrointestinal and genitourinary symptoms associated with anaphylaxis because of its relaxer effects on the smooth muscle of the stomach, intestine, uterus and urinary bladder.

When given intramuscularly or subcutaneously, epinephrine has a rapid onset and short duration of action.

13 NONCLINICAL TOXICOLOGY

13.1 Carcinogenesis, Mutagenesis, Impairment of Fertility

Long-term studies to evaluate the carcinogenic potential of epinephrine have not been conducted.

Epinephrine and other catecholamines have been shown to have mutagenic potential in vitro and to be an oxidative mutagen in a WP2 bacterial reverse mutation assay.

Epinephrine was positive in the DNA Repair test with B. subtilis (REC) assay, but was not mutagenic in the Salmonella bacterial reverse mutation assay.

The potential for epinephrine to impair fertility has not been evaluated.

This should not prevent the use of epinephrine under the conditions noted under INDICATIONS & USAGE (1).

16 HOW SUPPLIED/STORAGE & HANDLING

EPINEPHRINE INJECTION, USPis supplied in the following dosage forms.
NDC 51662-1222-1
EPINEPHRINE INJECTION, USP AUTO INJECTOR 0.15mg

NDC 51662-1223-1

EPINEPHRINE INJECTION, USP AUTO INJECTOR 0.30mg

HF Acquisition Co LLC, DBA HealthFirst

Mukilteo, WA 98275

Also supplied in the following manufacture supplied dosage forms

16.1 How Supplied

Carton containing two epinephrine injection, USP auto-injectors 0.3 mg: NDC 0115-1694-49.
Carton containing one epinephrine injection, USP auto-injector 0.3 mg: NDC 0115-1694-30.
Carton containing two epinephrine injection, USP auto-injectors 0.15 mg: NDC 0115-1695-49.
Carton containing one epinephrine injection, USP auto-injector 0.15 mg: NDC 0115-1695-30.

Rx only

16.2 Storage and Handling

Protect from light. Epinephrine is light sensitive and should be stored in the carrying-case provided to protect it from light. Store at room temperature (20° to 25°C (68° to 77°F)); excursions permitted to 15° to 30°C (59° to 86°F) [See USP Controlled Room Temperature]. Do not refrigerate. Before using, check to make sure the solution in the auto-injector is clear and colorless. Replace the auto-injector if the solution is discolored (pinkish or brown color), cloudy, or contains particles.

17 PATIENT COUNSELING INFORMATION

[see FDA-Approved Patient Labeling (PATIENT INFORMATION and INSTRUCTIONS FOR USE)]

A healthcare provider should review the patient instructions and operation of epinephrine injection, USP auto-injector, in detail, with the patient or caregiver.

Epinephrine is essential for the treatment of anaphylaxis. Carefully instruct patients who are at risk of or with a history of severe allergic reactions (anaphylaxis) to insect stings or bites, foods, drugs, and other allergens, as well as idiopathic and exercise-induced anaphylaxis, about the circumstances under which epinephrine should be used.

Administration and Training

Instruct patients and/or caregivers in the appropriate use of epinephrine injection, USP auto-injector. Epinephrine injection, USP auto-injector should be injected into the middle of the outer thigh (through clothing if necessary).

Instruct caregivers to hold the leg of young children firmly in place and limit movement prior to and during injection. Lacerations, bent needles, and embedded needles have been reported when epinephrine injection, USP auto-injector has been injected into the thigh of young children who are uncooperative and kick during an injection [see WARNINGS & PRECAUTIONS (5.2)].

Each epinephrine injection, USP auto-injector is a single-use injection. Advise patients to seek immediate medical care in conjunction with administration of epinephrine injection, USP auto-injector.

Complete patient information, including dosage, directions for proper administration and precautions can be found inside each epinephrine injection, USP auto-injector carton. A printed label on the surface of epinephrine injection, USP auto-injector shows instructions for use and a diagram depicting the injection process.

Instruct patients and/or caregivers to use the Trainer to familiarize themselves with the use of epinephrine injection, USP auto-injector in an allergic emergency. The Trainer may be used multiple times.

Adverse Reactions

Epinephrine may produce symptoms and signs that include an increase in heart rate, the sensation of a more forceful heartbeat, palpitations, sweating, nausea and vomiting, difficulty breathing, pallor, dizziness, weakness or shakiness, headache, apprehension, nervousness, or anxiety. These signs and symptoms usually subside rapidly, especially with rest, quiet, and recumbency. Patients with hypertension or hyperthyroidism may develop more severe or persistent effects, and patients with coronary artery disease could experience angina. Patients with diabetes may develop increased blood glucose levels following epinephrine administration. Patients with Parkinson's disease may notice a temporary worsening of symptoms [see WARNINGS & PRECAUTIONS (5.5)].

Accidental Injection

Advise patients to seek immediate medical care in the case of accidental injection. Since epinephrine is a strong vasoconstrictor when injected into the digits, hands or feet, treatment should be directed at vasodilation if there is such an accidental injection to these areas [see WARNINGS & PRECAUTIONS (5.2)].

Serious Infections at the Injection Site

Rare cases of skin and soft tissue infections, including necrotizing fasciitis and myonecrosis caused by Clostridia (gas gangrene), have been reported at the injection site following epinephrine injection for anaphylaxis. Advise patients to seek medical care if they develop signs or symptoms of infection, such as persistent redness, warmth, swelling, or tenderness, at the epinephrine injection site [see WARNINGS & PRECAUTIONS (5.3)].

Storage and Handling

Instruct patients to inspect the epinephrine solution visually through the viewing window periodically. Replace epinephrine injection, USP auto-injector if the epinephrine solution appears discolored (pinkish or brown), cloudy, or contains particles. Epinephrine is light sensitive, store in the outer case provided to protect it from light. Instruct patients that epinephrine injection, USP auto-injector must be properly disposed of once the blue caps have been removed or after use [see HOW SUPPLIED/STORAGE & HANDLING (16.2)].

Complete patient information, including dosage, directions for proper administration and precautions are provided inside each epinephrine injection, USP auto-injector carton.

Manf. by:
Hospira, Inc.
McPherson, KS 67460

Dist. by:
Impax Generics
Hayward, CA 94544

© 2016 Impax Laboratories, Inc., Hayward, CA. All rights reserved.

For inquiries call 1-800-934-6729
1871-02
Rev. 08/2018

PATIENT INFORMATION

EPINEPHRINE INJECTION, USP AUTO-INJECTOR (ep-in-eph-rine)

Authorized generic of Adrenaclick®

For allergic emergencies (anaphylaxis)

Read this Patient Information Leaflet carefully before you use the epinephrine injection, USP auto-injector, and each time you get a refill. There may be new information. You, your parent, caregiver, or others who may be in a position to administer epinephrine injection, USP auto-injector should know how to use it before you have an allergic emergency.

This information does not take the place of talking with your healthcare provider about your medical condition or your treatment.

What is the most important information I should know about epinephrine injection, USP auto-injector?

1. Epinephrine injection, USP auto-injector contains epinephrine, a medicine used to treat allergic emergencies (anaphylaxis). Anaphylaxis can be life-threatening, can happen within minutes, and can be caused by stinging and biting insects, allergy injections, foods, medicines, exercise, or other unknown causes. Symptoms of an anaphylaxis may include:

trouble breathing
wheezing
hoarseness (changes in the way your voice sounds)
hives (raised reddened rash that may itch)
severe itching
swelling of your face, lips, mouth, or tongue
skin rash, redness, or swelling
fast heartbeat
weak pulse
feeling very anxious
confusion
stomach pain
losing control of urine or bowel movements (incontinence)
diarrhea or stomach cramps
dizziness, fainting, or “passing out” (unconsciousness)

2. Always carry your epinephrine injection, USP auto-injector with you because you may not know when anaphylaxis may happen. Talk to your healthcare provider if you need additional units to keep at work, school, or other locations. Tell your family members, caregivers, and others where you keep your epinephrine injection, USP auto-injector and how to use it before you need it. You may be unable to speak in an allergic emergency.

3. When you have an allergic emergency (anaphylaxis)

Use epinephrine injection, USP auto-injector right away.
Get emergency medical help right away. You may need further medical attention. You may need to use a second epinephrine injection, USP auto-injector if symptoms continue or recur. Only a healthcare provider should give additional doses of epinephrine if you need more than 2 injections for a single anaphylaxis episode.

What is epinephrine injection, USP auto-injector?

Epinephrine injection, USP auto-injector is a disposable, prefilled automatic injection device (auto-injector) used to treat life-threatening, allergic emergencies including anaphylaxis in people who are at risk for or have a history of serious allergic emergencies. Each device contains a single dose of epinephrine.
Epinephrine injection, USP auto-injector is for immediate self (or caregiver) administration and does not take the place of emergency medical care. You should get emergency medical help right away after using epinephrine injection, USP auto-injector.
Epinephrine injection, USP auto-injector is for people who have been prescribed this medicine by their healthcare provider.
The epinephrine injection, USP auto-injector 0.3 mg auto-injector is for patients who weigh 66 pounds or more (30 kilograms or more).
The epinephrine injection, USP auto-injector 0.15 mg auto-injector is for patients who weigh about 33 to 66 pounds (15 to 30 kilograms).
It is not known if epinephrine injection, USP auto-injector is safe and effective in children who weigh less than 33 pounds (15 kilograms).

What should I tell my healthcare provider before using epinephrine injection, USP auto-injector?

Before you use epinephrine injection, USP auto-injector, tell your healthcare provider about all your medical conditions, especially if you:

have heart problems or high blood pressure
have diabetes
have thyroid problems
have asthma
have a history of depression
have Parkinson's disease
have any other medical conditions
are pregnant or plan to become pregnant. It is not known if epinephrine will harm your unborn baby.
are breastfeeding or plan to breastfeed. It is not known if epinephrine passes into your breast milk.

Tell your healthcare provider about all the medicines you take, including prescription and over-the-counter medicines, vitamins and herbal supplements. Tell your healthcare provider of all known allergies.

Especially tell your healthcare provider if you take certain asthma medicines.

Epinephrine injection, USP auto-injector and other medicines may affect each other, causing side effects. Epinephrine injection, USP auto-injector may affect the way other medicines work, and other medicines may affect how epinephrine injection, USP auto-injector works.

Know the medicines you take. Keep a list of them to show your healthcare provider and pharmacist when you get a new medicine.

Use your epinephrine injection, USP auto-injector for treatment of anaphylaxis as prescribed by your healthcare provider, regardless of your medical conditions or the medicine you take.

How should I use epinephrine injection, USP auto-injector?

Each epinephrine injection, USP auto-injector contains only 1 dose of medicine.
Epinephrine injection, USP auto-injector should only be injected into the middle of the outer thigh (upper leg). It can be injected through clothing, if needed.
Read the Instructions for Use at the end of this Patient Information Leaflet for information about the right way to use epinephrine injection, USP auto-injector.
Your healthcare provider will show you how to safely use the epinephrine injection, USP auto-injector.
Use epinephrine injection, USP auto-injector exactly as your healthcare provider tells you to use it. You may need to use a second epinephrine injection, USP auto-injector if symptoms continue or recur. Only a healthcare provider should give additional doses of epinephrine if you need more than 2 injections for a single anaphylaxis episode.
Caution: Never put your thumb, fingers, or hand over the red tip. Never press or push the red tip with your thumb, fingers, or hand. The needle comes out of the red tip. Accidental injection into finger, hands, or feet may cause a loss of blood flow to those areas. If this happens, go immediately to the nearest emergency room. Tell the healthcare provider where on your body you received the accidental injection.
Your epinephrine injection, USP auto-injector comes packaged in a carton containing 1 or 2 epinephrine injection, USP auto-injectors.
You may request a separate Trainer, that comes packaged with instructions. Additional video instructions on the use of epinephrine injection, USP auto-injector are available from www.epinephrineautoinject.com. The epinephrine injection, USP auto-injector Trainer has a beige color. The beige epinephrine injection, USP auto-injector Trainer contains no medicine and no needle. Practice with your epinephrine injection, USP auto-injector Trainer before an allergic emergency happens to make sure you are able to safely use the real epinephrine injection, USP auto-injector in an emergency. Always carry your real epinephrine injection, USP auto-injector with you in case of an allergic emergency.
Do not drop the carrying case or epinephrine injection, USP auto-injector. If the carrying case or epinephrine injection, USP auto-injector is dropped, check for damage and leakage. Dispose of the auto-injector and carrying case, and replace if damage or leakage is noticed or suspected.

What are the possible side effects of epinephrine injection, USP auto-injector?

Epinephrine injection, USP auto-injector may cause serious side effects.

Epinephrine injection, USP auto-injector should only be injected into the middle of your outer thigh (upper leg). Do not inject epinephrine injection, USP auto-injector into your:

veins
buttocks
fingers, toes, hands or feet.

If you accidently inject epinephrine injection, USP auto-injector into any other part of your body, go to the nearest emergency room right away. Tell the healthcare provider where on your body you received the accidental injection.

Rarely, patients who use epinephrine injection, USP auto-injector may develop infections at the injection site within a few days of an injection. Some of these infections can be serious. Call your healthcare provider right away if you have any of the following at an injection site:

redness that does not go away
swelling
tenderness
the area feels warm to the touch

Cuts on the skin, bent needles, and needles that remain in the skin after the injection, have happened in young children who do not cooperate and kick or move during an injection. If you inject a young child with epinephrine injection, USP auto-injector, hold their leg firmly in place before and during the injection to prevent injuries. Ask your healthcare provider to show you how to properly hold the leg of a young child during an injection.
If you have certain medical conditions, or take certain medicines, your condition may get worse or you may have more or longer lasting side effects when you use epinephrine injection, USP auto-injector. Talk to your healthcare provider about all your medical conditions.

Common side effects of epinephrine injection, USP auto-injector include:

faster, irregular or “pounding” heartbeat
sweating
headache
weakness
shakiness
paleness
feelings of over excitement, nervousness, or anxiety
dizziness
nausea or vomiting
breathing problems

These side effects may go away with rest. Tell your healthcare provider if you have any side effect that bothers you or that does not go away.

These are not all the possible side effects of epinephrine injection, USP auto-injector. For more information, ask your healthcare provider or pharmacist.

Call your healthcare provider for medical advice about side effects. You may report side effects to FDA at 1-800-FDA-1088.

How should I store epinephrine injection, USP auto-injector?

Store epinephrine injection, USP auto-injector at room temperature between 68° to 77° F (20° to 25° C).
Protect from light.
Do not expose to extreme heat or cold. For example, do not store in your vehicle’s glove box and do not store in the refrigerator or freezer.
Examine the contents in the clear viewing window of your auto-injector periodically. The solution should be clear. If the solution is discolored (pinkish or brown), cloudy or contains solid particles, replace the unit.
Always keep your epinephrine injection, USP auto-injector in the carrying case to protect it from damage; however, the carrying case is not waterproof.
The two blue end caps help to prevent accidental injection. Do not remove the blue end caps until you are ready to use epinephrine injection, USP auto-injector.
Your epinephrine injection, USP auto-injector has an expiration date. Replace it before the expiration date.

Keep epinephrine injection, USP auto-injector and all medicines out of the reach of children.

General information about the safe and effective use of epinephrine injection, USP auto-injector:

Medicines are sometimes prescribed for purposes other than those listed in a Patient Information Leaflet. Do not use epinephrine injection, USP auto-injector for a condition for which it was not prescribed. Do not give epinephrine injection, USP auto-injector to other people.

This Patient Information Leaflet summarizes the most important information about epinephrine injection, USP auto-injector. If you would like more information, talk to your healthcare provider. You can ask your pharmacist or healthcare provider for information about epinephrine injection, USP auto-injector that is written for health professionals.

For more information and video instructions on the use of epinephrine injection, USP auto-injector, go to www.epinephrineautoinject.com or call 1-800-934-6729.

What are the ingredients in epinephrine injection, USP auto-injector?

Active Ingredient: epinephrine

Inactive Ingredients: sodium chloride, chlorobutanol, sodium bisulfite, hydrochloric acid and sodium hydroxide, and water.

Important Information

The epinephrine injection, USP auto-injector 0.3 mg auto-injector has a yellow colored label.
The epinephrine injection, USP auto-injector 0.15 mg auto-injector has an orange colored label.
The epinephrine injection, USP auto-injector Trainer has a beige color, and contains no medicine and no needle.
Your auto-injector is designed to work through clothing.
The two blue end caps on the epinephrine injection, USP auto-injector help to prevent accidental injection of the device. Do not remove the blue end caps until you are ready to use it.
Only inject into the middle of the outer thigh (upper leg). Never inject into any other part of the body.
Never put your thumb, fingers, or your hand over the red tip. The needle comes out of the red tip.
If an accidental injection happens, get medical help right away.
Do not place patient information or any other foreign objects in carrier with the auto-injector, as this may prevent you from removing the auto-injector for use.

INSTRUCTIONS FOR USE

EPINEPHRINE INJECTION, USP AUTO-INJECTOR (ep-in-eph-rine)

For allergic emergencies (anaphylaxis)

Read these Instructions for Use carefully before you use epinephrine injection, USP auto-injector. Before you need to use your epinephrine injection, USP auto-injector, make sure your healthcare provider shows you the right way to use it. Parents, caregivers, and others who may be in a position to administer epinephrine injection, USP auto-injector should also understand how to use it well. If you have any questions, ask your healthcare provider.

Your epinephrine injection, USP auto-injector

STEP 1. Prepare epinephrine injection, USP auto-injector for injection

Remove epinephrine injection, USP auto-injector from its protective carrying case.
Pull off blue end caps; you will now see a red tip. Grasp the auto-injector in your fist with the red tip pointing downward. See Figure A.

Note:

The needle comes out of the red tip.
To avoid an accidental injection, never put your thumb, fingers, or hand over the red tip. If an accidental injection happens, get medical help right away.

STEP 2. Administer epinephrine injection, USP auto-injector

If you are administering epinephrine injection, USP auto-injector to a young child, hold the leg firmly in place and limit movement prior to and while administering an injection.
Put the red tip against the middle of the outer thigh (upper leg) at a 90° angle (perpendicular) to the thigh.
Press down hard and hold firmly against the thigh for approximately 10 seconds to deliver the medicine. See Figure B.

Only inject into the middle of the outer thigh. Do not inject into any other part of the body.
Remove epinephrine injection, USP auto-injector from the thigh.
Massage the area for 10 seconds.
Check the red tip. The injection is complete and you have received the correct dose of the medicine if you see the needle sticking out of the red tip. If you do not see the needle repeat Step 2.

STEP 3. Get emergency medical help right away. You may need further medical attention. You may need to use a second epinephrine injection, USP auto-injector if symptoms continue or recur.

STEP 4. After use / Disposal

Carefully cover the needle with the carrying case.

Lay the labeled half of the carrying case cover down on a flat surface. Use one hand to carefully slide the end of the auto-injector, needle first, into the labeled carrying case cover. See Figure C.

After the needle is inside the labeled cover, push the unlabeled half of the carrying case cover firmly over the non-needle end of the auto-injector. See Figure D.

Take your used epinephrine injection, USP auto-injector with you when you go to see a healthcare provider.
Tell the healthcare provider that you have received an injection of epinephrine. Show the healthcare provider where you received the injection.
Give your used epinephrine injection, USP auto-injector to the healthcare provider for inspection and proper disposal.
Ask for a refill, if needed.

Note:

Epinephrine injection, USP auto-injector is a single-use injectable device that delivers a fixed dose of epinephrine. The auto-injector cannot be reused. Do not attempt to reuse epinephrine injection, USP auto-injector after the device has been activated. It is normal for most of the medicine to remain in the auto-injector after the dose is injected. The correct dose has been administered if you see the needle sticking out of the red tip.
A separate epinephrine injection, USP auto-injector Trainer is available. The epinephrine injection, USP auto-injector Trainer has a beige color. The beige epinephrine injection, USP auto-injector Trainer contains no medicine and no needle. Practice with your epinephrine injection, USP auto-injector Trainer, but always carry your real epinephrine injection, USP auto-injector in case of an allergic emergency.
If you will be administering epinephrine injection, USP auto-injector to a young child, ask your healthcare provider to show you how to properly hold the leg in place while administering a dose.
Do not try to take the epinephrine injection, USP auto-injector apart.

For more information and video instructions on the use of epinephrine injection, USP auto-injector, go to www.epinephrineautoinject.com or call 1-800-934-6729.

This Patient Information and Instructions for Use has been approved by the U.S. Food and Drug Administration.

© 2016 Impax Laboratories, Inc., Hayward, CA. All rights reserved.

Manf. by:
Hospira, Inc.
McPherson, KS 67460

Dist. by:
Impax Generics
Hayward, CA 94544

1872-02
Rev. 08/2018

PRINCIPLE DISPLAY PANEL, 0.15 mL CASE LABEL

PRINCIPAL DISPLAY PANEL - 0.15 mg CASE LABEL
epinephrine injection, USP
auto-injector
0.15 mg
Impax Generics

PRINCIPLE DISPLAY PANEL, 0.3 ml case label

PRINCIPAL DISPLAY PANEL - 0.3 mg CASE LABEL
epinephrine injection, USP
auto-injector
0.3 mg
Impax Generics